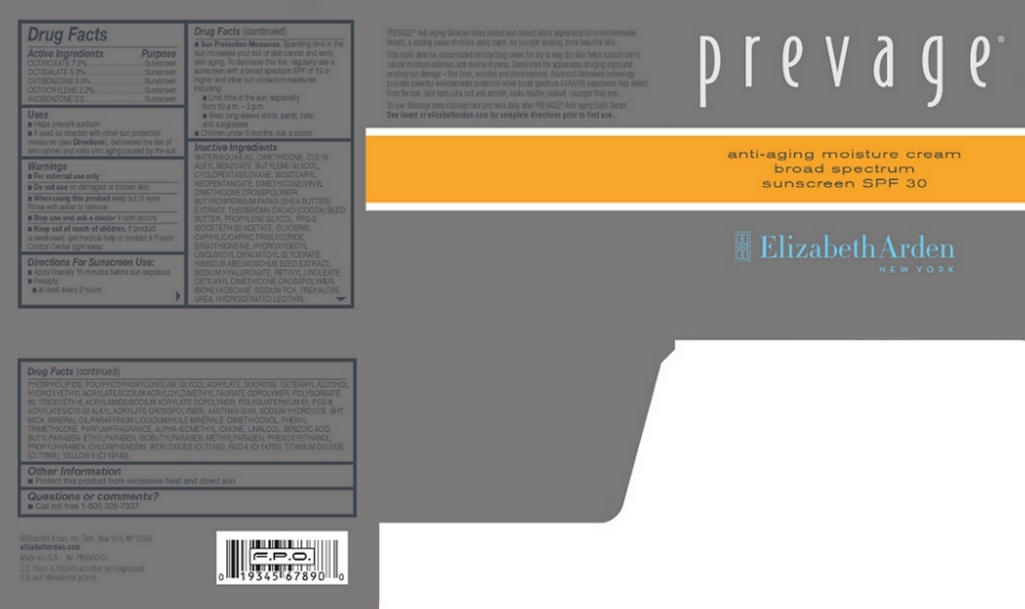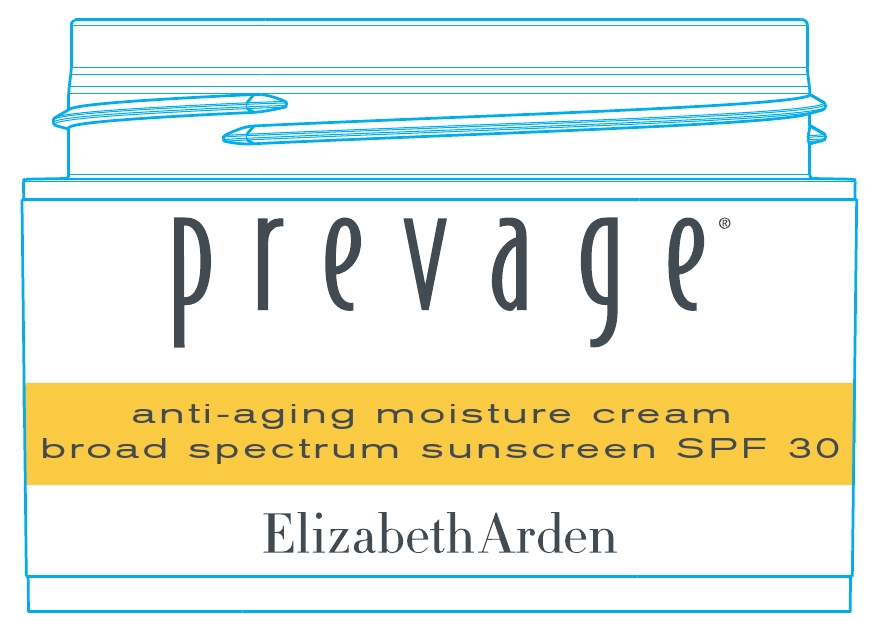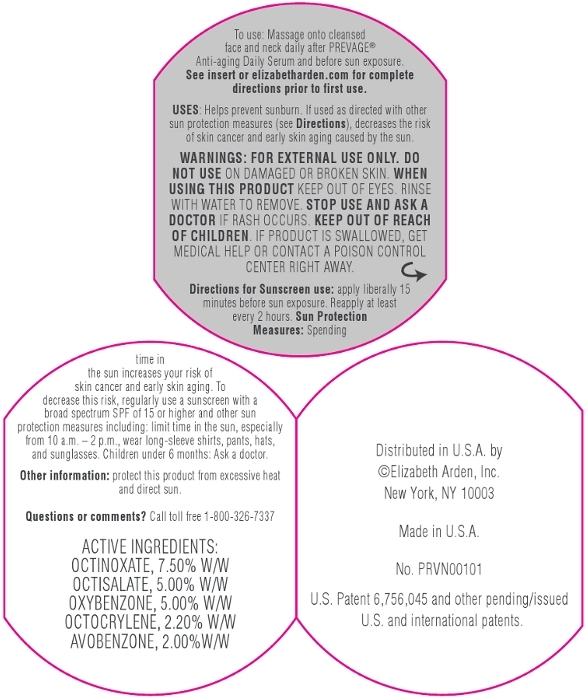 DRUG LABEL: Prevage Anti Aging Moisture Broad Spectrum Sunscreen SPF 30
NDC: 67938-9144 | Form: CREAM
Manufacturer: Elizabeth Arden, Inc
Category: otc | Type: HUMAN OTC DRUG LABEL
Date: 20130501

ACTIVE INGREDIENTS: OCTINOXATE 3.75 g/50 g; OCTISALATE 2.5 g/50 g; OXYBENZONE 2.5 g/50 g; OCTOCRYLENE 1.1 g/50 g; AVOBENZONE 1 g/50 g
INACTIVE INGREDIENTS: WATER; DIMETHICONE; BUTYLENE GLYCOL; ISOSTEARYL NEOPENTANOATE; PROPYLENE GLYCOL; PPG-2 ISOCETETH-20 ACETATE; GLYCERIN; ERGOTHIONEINE; ISOHEXADECANE; TREHALOSE; SUCROSE; POLYSORBATE 60; TRIDECETH-6; XANTHAN GUM; SODIUM HYDROXIDE; MICA; MINERAL OIL; PHENYL TRIMETHICONE; BENZOIC ACID; BUTYLPARABEN; ETHYLPARABEN; ISOBUTYLPARABEN; METHYLPARABEN; PHENOXYETHANOL; PROPYLPARABEN; CHLORPHENESIN

BC1144

DESCRIPTION

PREVAGE® Anti-aging Skincare helps protect and correct skin’s appearance from environmental threats, a leading cause of visible aging signs, for younger-looking, more beautiful skin. This multi-defense, concentrated moisturizing cream for dry to very dry skin helps nourish skin’s natural moisture defenses and reverse dryness. Diminishes the appearance of aging signs and existing sun damage – fine lines, wrinkles and discolorations. Advanced Idebenone technology provides powerful environmental protection while broad spectrum UVA/UVB sunscreens help shield from the sun. Skin feels ultra soft and smooth, looks healthy, radiant - younger than ever.

INDICATIONS AND USAGE

To Use: Massage onto cleansed face and neck daily after PREVAGE Anti-aging Daily Serum.Directions For Sunscreen Use: Apply liberally 15 minutes before sun exposure. Reapply at least every 2 hours.

Sun Protection Measures: Spending time in the sun increases your risk of skin cancer and early skin aging. To decrease this risk, regularly use a sunscreen with a broad spectrum SPF of 15 or higher and other sun protection measures including: Limit time in the sun, especially from 10 a.m. – 2 p.m. Wear long-sleeve shirts, pants, hats, and sunglasses.

Children under 6 months: Ask a doctor.

WARNINGS

For external use only

Do not use on damaged or broken skin

When using this product keep out of eyes. Rinse with water to remove.

Stop use and ask a doctor if rash occurs

OTC - ACTIVE INGREDIENT

Active Ingredients: Octinoxate 7.50%, Octisalate 5.00%, Oxybenzone 5.00%, Octocrylene 2.20%, Avobenzone 2.00%

INACTIVE INGREDIENT

Inactive Ingredients: Water/Aqua/Eau, Dimethicone, C12-15 Alkyl Benzoate, Butylene Glycol, Cyclopentasiloxane, Isostearyl Neopentanoate, Dimethicone/Vinyl Dimethicone Crosspolymer, Butyrospermum Parii (Shea Butter) Extract, Theobroma Cacao (Cocoa) Seed Butter, Propylene Glycol, PPG-2 Isoceteth-20 Acetate, Glycerin, Caprylic/Capric Triglyceride, Ergothioneine, Hydroxydecyl Ubiquinoyl Dipalmitoyl Glycerate, Hibiscus Abelmoschus Seed Extract, Sodium Hyaluronate, Retinyl Linoleate, Cetearyl Dimethicone Crosspolymer, Isohexadecane, Sodium PCA, Trehalose, Urea, Hydrogenated Lecithin, Phospholipids, Polyphosphorylcholine Glycol Acrylate, Sucrose, Cetearyl Alcohol, Hydroxyethyl Acrylate/Sodium Acryloyldimethyl Taurate Copolymer, Polysorbate 60, Trideceth-6, Acrylamide/Sodium Acrylate Copolymer, Polyquaternium-51, PEG-8, Acrylates/C10-30 Alkyl Acrylate Crosspolymer, Xanthan Gum, Sodium Hydroxide, BHT, Mica, Mineral Oil/Paraffinum Liquidum/Huile Minerale, Dimethiconol, Phenyl Trimethicone, Parfum/Fragrance, Alpha-Isomethyl Ionone, Linalool, Benzoic Acid, Butylparaben, Ethylparaben, Isobutylparaben, Methylparaben, Phenoxyethanol, Propylparaben, Chlorphenesin, Iron Oxides (CI 77492), Red 4 (CI 14700), Titanium Dioxide (CI 77891), Yellow 5 (CI 19140).

DOSAGE AND ADMINISTRATION

Massage onto face and neck.

OTC - KEEP OUT OF REACH OF CHILDREN

Keep out of reach of children. If product is swallowed, get medical help or contact a Poison Control Center right away.

OTC - PURPOSE

Provides SPF 30 Sun Protection.

OTC - WHEN USING

Keep out of eyes.